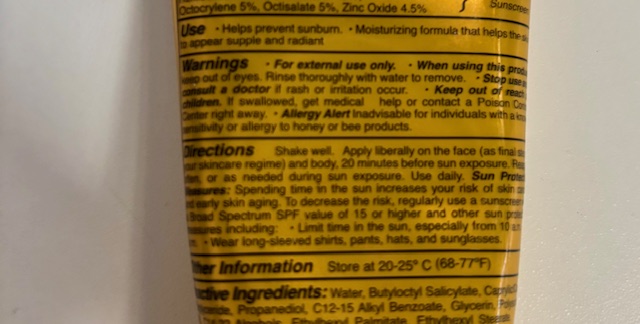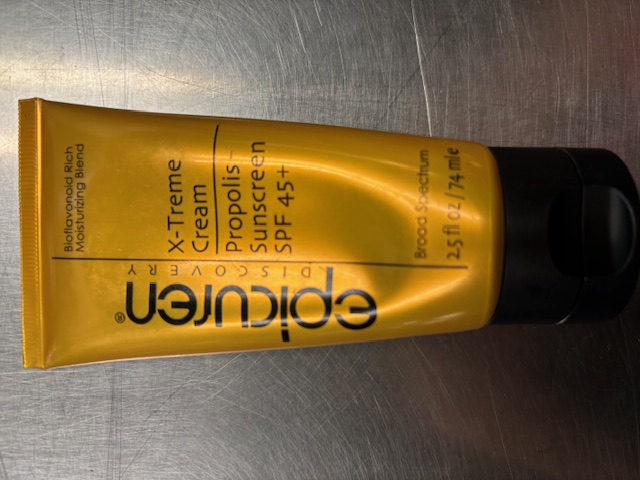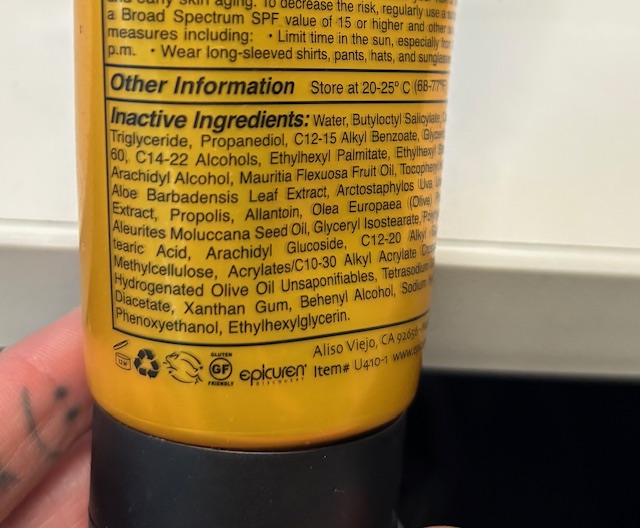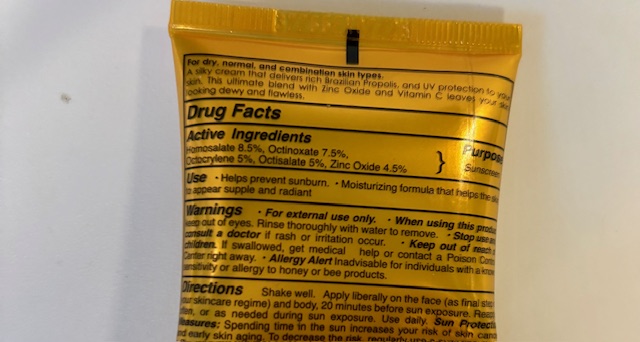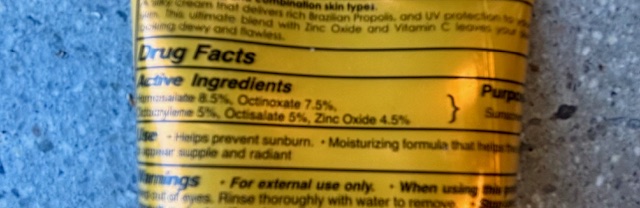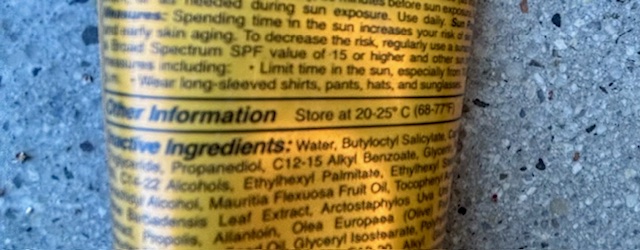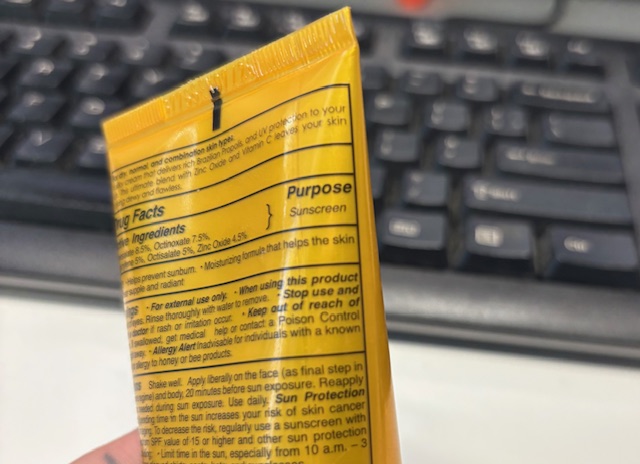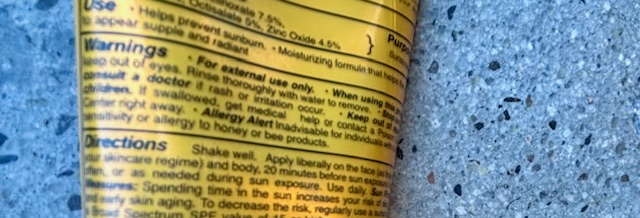 DRUG LABEL: X-Treme Cream Propolis Sunscreen SPF 45
NDC: 84378-101 | Form: CREAM
Manufacturer: Epicuren Discovery
Category: otc | Type: HUMAN OTC DRUG LABEL
Date: 20251002

ACTIVE INGREDIENTS: ZINC OXIDE 4.5 g/100 g; OCTISALATE 5 g/100 g; OCTINOXATE 7.5 g/100 g; OCTOCRYLENE 5 g/100 g; HOMOSALATE 8.5 g/100 g
INACTIVE INGREDIENTS: PHENOXYETHANOL; PROPOLIS WAX; SODIUM HYDROXIDE; ETHYLHEXYLGLYCERIN; WATER; ALEURITES MOLUCCANA SEED; C12-20 ALKYL GLUCOSIDE; HYDROGENATED OLIVE OIL; GLYCERIN; ACRYLATES/C10-30 ALKYL ACRYLATE CROSSPOLYMER (60000 MPA.S); METHYLCELLULOSE; BUTYLOCTYL SALICYLATE; POLYSORBATE 60; ETHYLHEXYL PALMITATE; MAURITIA FLEXUOSA FRUIT OIL; ARACHIDYL GLUCOSIDE; ALLANTOIN; C12-15 ALKYL BENZOATE; C14-22 ALCOHOLS; ETHYLHEXYL STEARATE; POLYHYDROXYSTEARIC ACID (2300 MW); ALOE BARBADENSIS LEAF; XANTHAN GUM; .ALPHA.-TOCOPHEROL ACETATE; TETRASODIUM GLUTAMATE DIACETATE; GLYCERYL ISOSTEARATE; BEHENYL ALCOHOL; ARCTOSTAPHYLOS UVA-URSI LEAF; 1,3-PROPANEDIOL BIS(4-AMINOBENZOATE); OLEA EUROPAEA (OLIVE) FRUIT OIL; CAPRYLIC/CAPRIC TRIGLYCERIDE; ARACHIDYL ALCOHOL

X-treme Cream Propolis Sunscreen SPF45